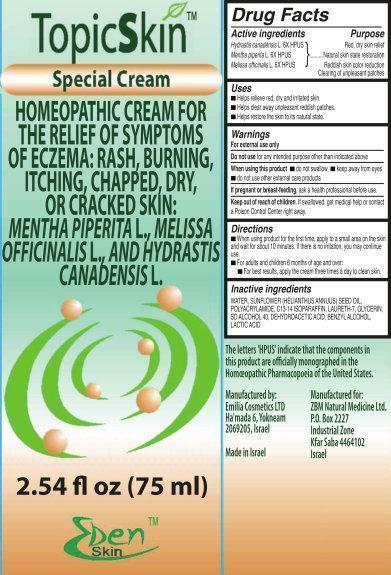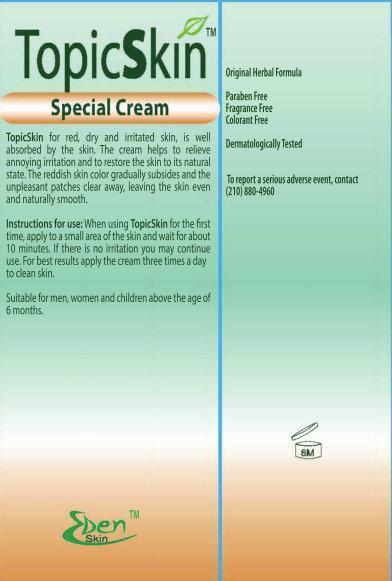 DRUG LABEL: TopicSkin 
NDC: 69121-001 | Form: CREAM
Manufacturer: ZBM Natural Medicine Ltd.
Category: homeopathic | Type: HUMAN OTC DRUG LABEL
Date: 20141110

ACTIVE INGREDIENTS: HYDRASTIS CANADENSIS WHOLE 6 [hp_X]/1 mL; MENTHA PIPERITA 6 [hp_X]/1 mL; MELISSA OFFICINALIS 6 [hp_X]/1 mL
INACTIVE INGREDIENTS: WATER; SUNFLOWER OIL; POLYACRYLAMIDE (10000 MW); C13-14 ISOPARAFFIN; LAURETH-7; GLYCERIN; DEHYDROACETIC ACID; BENZYL ALCOHOL; LACTIC ACID

TopicSkin

Active Ingredients

Hydrastis canadensis L. 6X HPUS

Mentha piperita L. 6X HPUS

Melissa officinalis L. 6X HPUS

Purpose

Red, dry skin relief

Natural skin state restoration

Reddish skin color reduction Clearing of unpleasant patches

Uses

Helps relieve red, dry and irritated skin.

Helps clear away unpleasant reddish patches.

Helps restore the skin to its natural state.

Warnings

For external use only

Do not use

for any intended purpose other than indicated above.

When using this product

do not swallow keep away from eyes

do not use other external care products

If pregnant or breast-feeding

ask a health professional before use.

Keep out of reach of children

If swallowed, get medical help or contact a Poison Control Center right away.

Directions

When using product for the first time, apply to a small area on the skin and wait for about 10 minutes. If there is no irritation, you may continue use.

For adults and children 6 months of age and over

For best results, apply the cream three times a day to clean skin.

Inactive Ingredients

WATER, SUNFLOWER (HELIANTHUS ANNUUS) SEED OIL, POLYACRYLAMIDE, C13-14 ISOPARAFFIN, LAURETH-7, GLYCERIN, SD ALCOHOL 40, DEHYDROACETIC ACID, BENZYL ALCOHOL, LACTIC ACID

The letters H.P.U.S. indicate that the components in this product are officially monographed in the Homeopathic Pharmacopoeia of the U.S. The letters ER indicate Eczema Relief.

Manufactured by:

Emilia Cosmetics LTD

Ha'mada 6, Yokneam

2069205, Israel

Made in Israel

Manufactured for:

ZBM Natural Medicine Ltd.

P.O. Box 2227

Industrial Zone

Kfar Saba 4464102

Israel

Package Label

TopicSkin

Special Cream

HOMEOPATHIC CREAM FOR THE RELIEF OF SYMPTOMS OF ECZEMA: RASH, BURNING, ITCHING, CHAPPED, DRY, OR CRACKED SKIN: MENTHA PIPERITA L., MELISSA OFFICINALIS L., AND HYDRASTIS CANADENSIS L.

2.54fl oz (75ml)

Original Herbal Formula

Paraben Free

Fragrance Free

Colorant Free

Dermatologically Tested

To report a serious adverse event, contact

(210) 880-4960